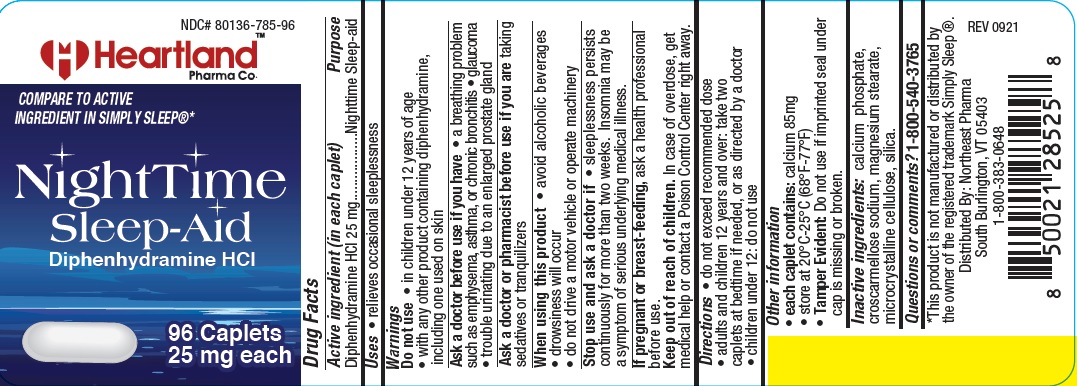 DRUG LABEL: Nighttime Sleep-aid
NDC: 80136-785 | Form: TABLET
Manufacturer: NORTHEAST PHARMA
Category: otc | Type: HUMAN OTC DRUG LABEL
Date: 20250515

ACTIVE INGREDIENTS: DIPHENHYDRAMINE HYDROCHLORIDE 25 mg/1 1
INACTIVE INGREDIENTS: SILICON DIOXIDE; CROSCARMELLOSE SODIUM; CELLULOSE, MICROCRYSTALLINE; CALCIUM PHOSPHATE, DIBASIC, ANHYDROUS; MAGNESIUM STEARATE

hpc 785

Active ingredient (in each caplet)

Diphenhydramine Hydrochloride 25mg

Purpose

Nighttime Sleep-aid

Uses

- relieves occasional sleeplessness

Warnings

Do not use

• in children under 12 years

• with any other product containing diphenhydramine, including one used

on skin

Ask a doctor before use if you have

• a breathing problem such as emphysema, asthma, or chronic bronchitis

• glaucoma

• trouble urinating due to an enlarged prostate gland

Ask a doctor or pharmacist before use if you are taking sedatives or tranquilizers

When using this product

• avoid alcoholic beverages

• drowsiness will occur

• do not drive a motor vehicle or operate machinery

Stop use and ask a doctor if • sleeplessness persists continuously for more than two weeks. Insomnia may be a symptom of serious underlying medical illness.

If pregnant or breast-feeding, ask a health professional before use.

Keep out of reach of children. In case of overdose, get medical help or contact a Poison Control Center right away.

Directions

• adults and children 12 years and over: take two caplets at bedtime if needed, or as directed by a doctor

• do not exceed recommended dose

Other information

- each caplet contains: calcium 85mg
- store at 20°C-25°C (68°F-77°F)
- Tamper Evident: Do not use if imprinted seal under cap is missing or broken.

Inactive ingredients

calcium phosphate, croscarmellose sodium, magnesium stearate,

microcrystalline cellulose, silica.

Questions or comments?

1-800-540-3765